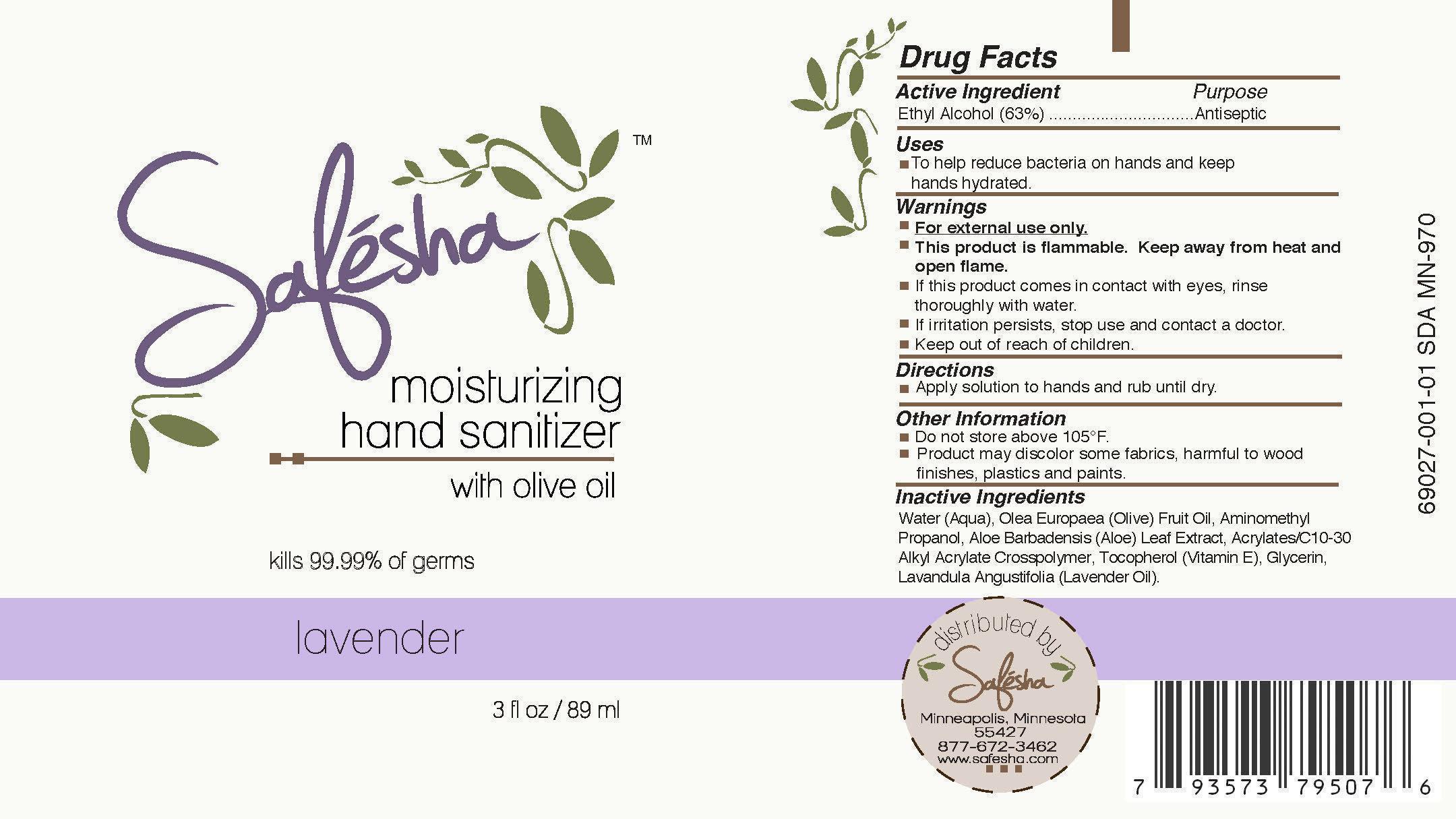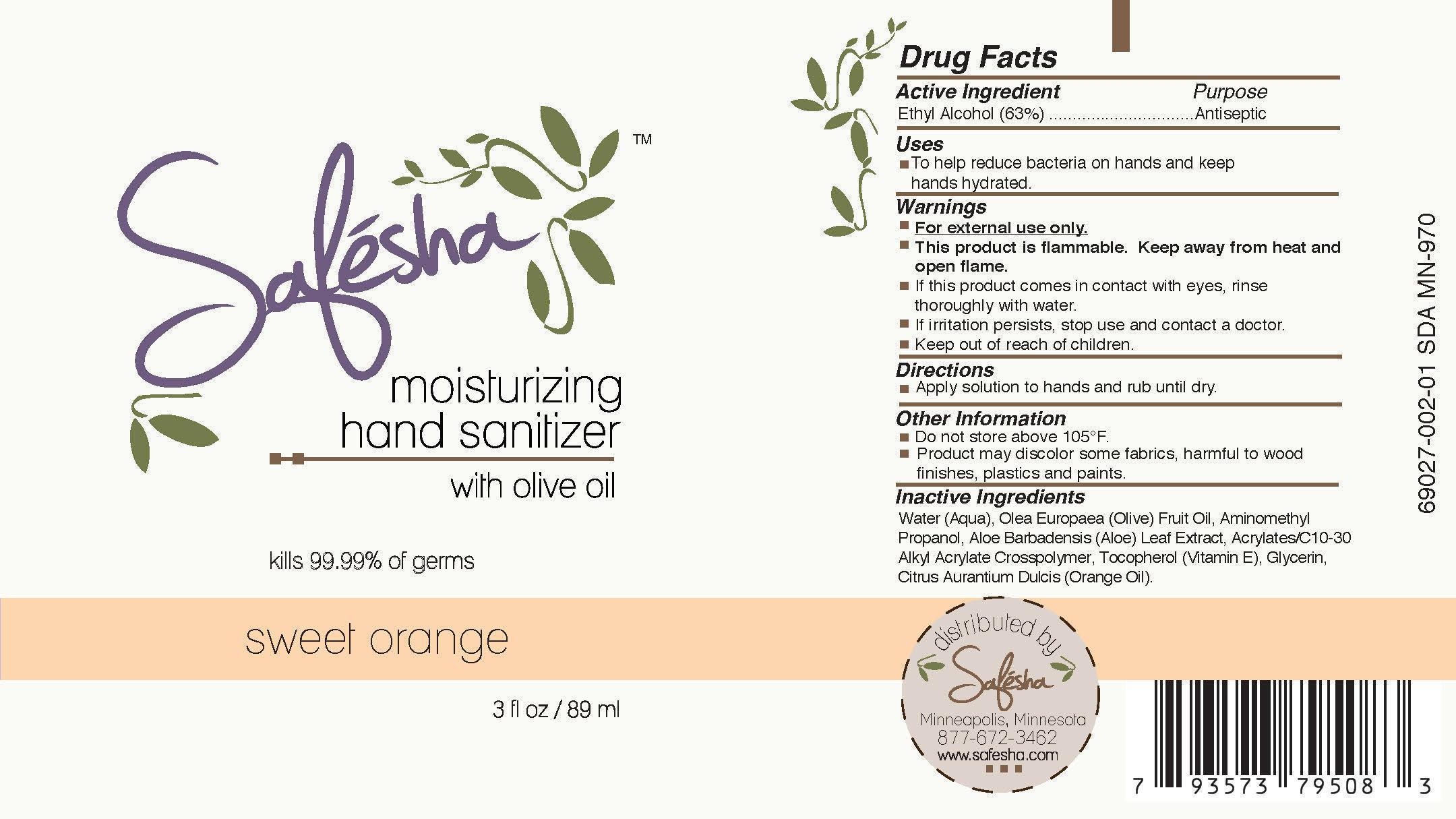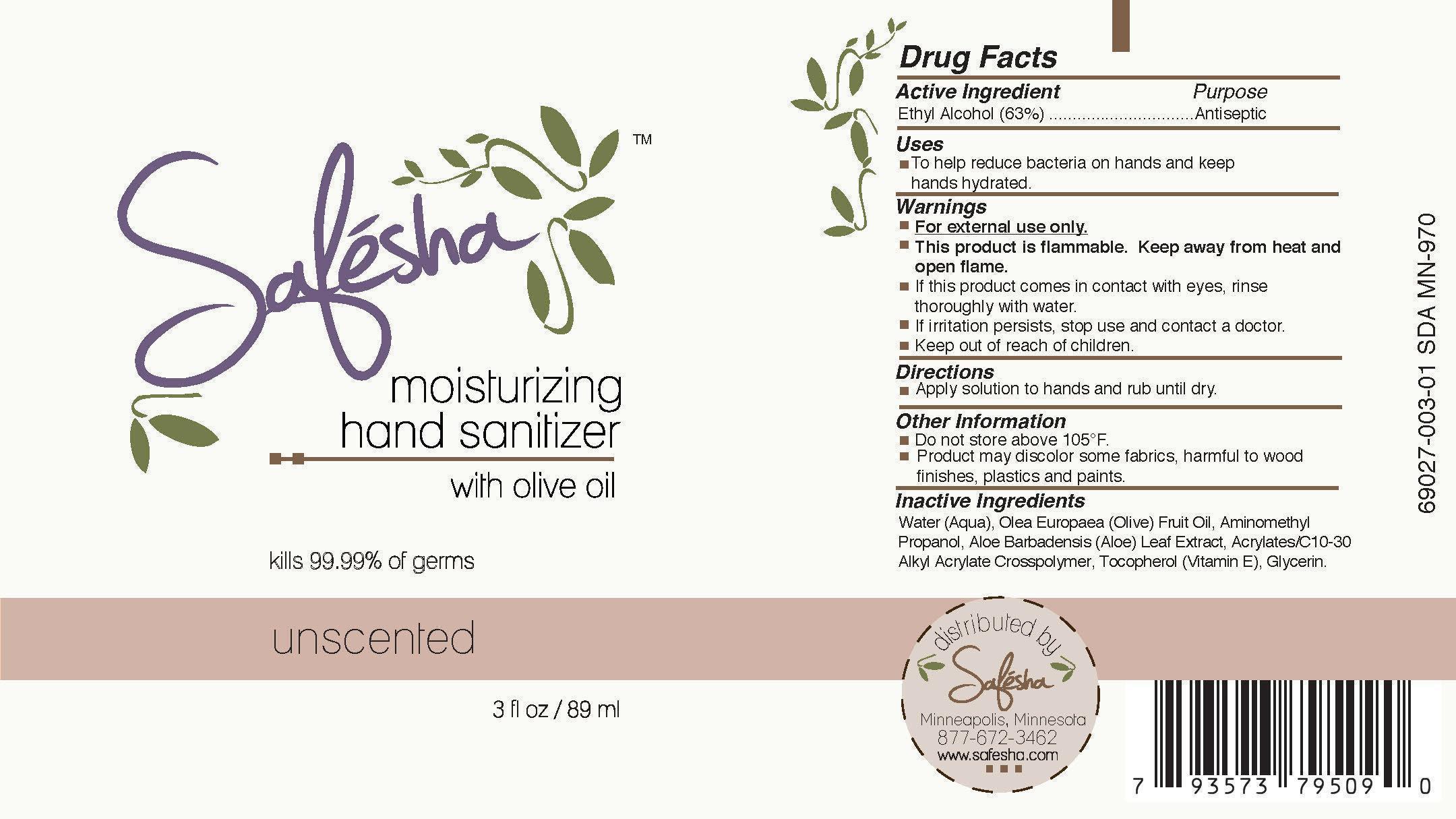 DRUG LABEL: Safesha
NDC: 69027-001 | Form: LIQUID
Manufacturer: Safesha, LLC
Category: otc | Type: HUMAN OTC DRUG LABEL
Date: 20211227

ACTIVE INGREDIENTS: ALCOHOL 56.07 1/56.07 1
INACTIVE INGREDIENTS: GLYCERIN; ALOE; TOCOPHEROL; WATER; AMINOMETHYL PROPANEDIOL; OLEA EUROPAEA FRUIT VOLATILE OIL; LAVENDER OIL

Warnings

<p class="First"><span style="text-decoration: underline;"><strong>For external use only.</strong></span></p><p class="First"><strong>This product is flammable. Keep away from heat and open flame.</strong><span style="text-decoration: underline;"><strong></strong></span></p><p class="First">If this product comes in contact with eyes, rinse thoroughly with water.</p><p class="First">If irritation persists, stop use and contact a doctor.</p><p class="First">Keep out of reach of children<br></p>

Image Components: White tube with purple cap and wrap label.

DOSAGE AND ADMINISTRATION

Apply solution to hands and rub until dry.

WARNINGS

Apply solution to hand and rub until dry.

INACTIVE INGREDIENT

Apply solution to hands and rub until dry.

INDICATIONS AND USAGE

Apply solution to hands and rub until dry.

INDICATIONS AND USAGE

Apply solution to hands and rub until dry.

PURPOSE

Apply solution to hands and rub until dry.

KEEP OUT OF REACH OF CHILDREN

Apply solution to hands and rub until dry.

ACTIVE INGREDIENT

Apply solution to hands and rub until dry.

Safesha Moisturizing Hand Sanitizer with Olive Oil (Lavender)

Kills 99.99% of germs

3 fl. oz. / 89 ml

Uses: To help reduce bacteria on hands and keep hands hydrated.

Directions: Apply solution to hands and rub until dry.

Other Information: Do not store above 105

Safesha Moisturizing Hand Sanitizer with Olive Oil (Sweet Orange)

Kills 99.99% of germs

3 fl. oz. / 89 ml

Uses: To help reduce bacteria on hands and keep hands hydrated.

Directions: Apply solution to hands and rub until dry.

Other Information: Do not store above 105

Safesha Moisturizing Hand Sanitizer with Olive Oil (Unscented)

Kills 99.99% of germs

3 fl. oz. / 89 ml

Uses: To help reduce bacteria on hands and keep hands hydrated.

Directions: Apply solution to hands and rub until dry.

Other Information: Do not store above 105